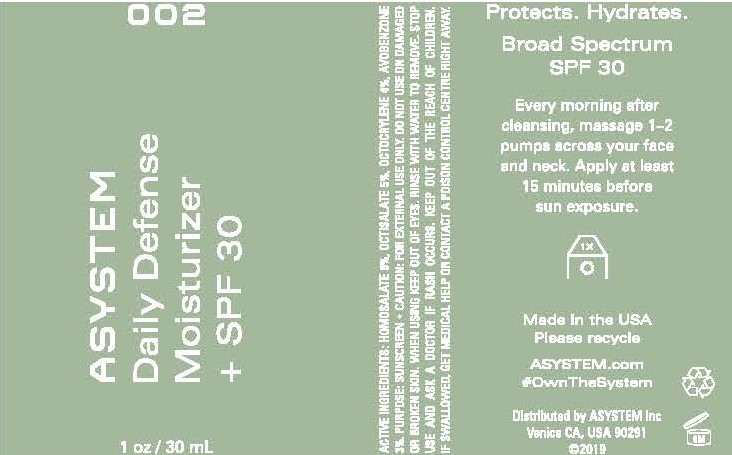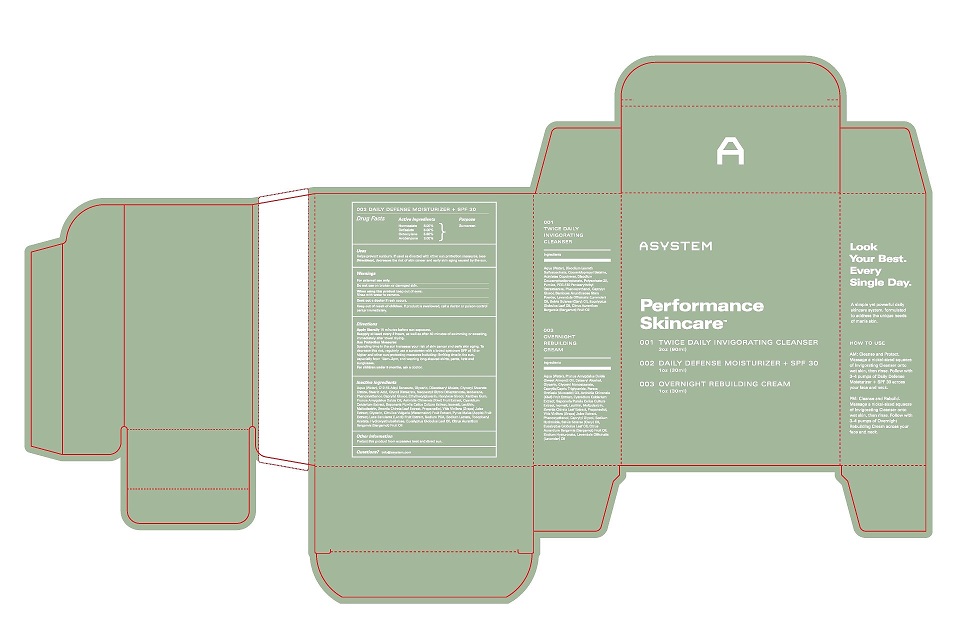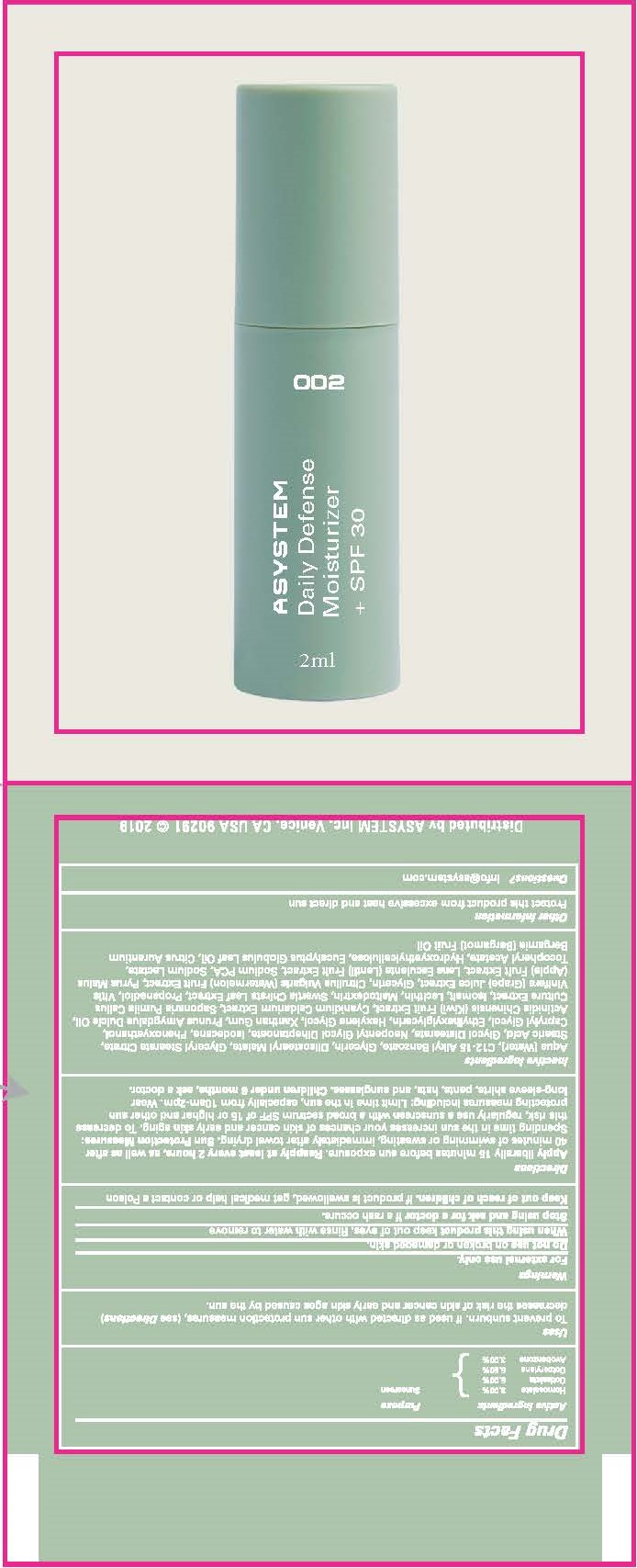 DRUG LABEL: ASYSTEM Daily Defense Moisturizer SPF30
NDC: 52261-4900 | Form: LOTION
Manufacturer: Cosco International, Inc.
Category: otc | Type: HUMAN OTC DRUG LABEL
Date: 20220214

ACTIVE INGREDIENTS: HOMOSALATE 0.08 kg/1 kg; OCTISALATE 0.05 kg/1 kg; OCTOCRYLENE 0.055 kg/1 kg; AVOBENZONE 0.03 kg/1 kg
INACTIVE INGREDIENTS: ALKYL (C12-15) BENZOATE; CAPRYLYL GLYCOL; CITRUS AURANTIUM FRUIT OIL; PHYMATOLITHON CALCAREUM; XANTHAN GUM; HYDROXYETHYL CELLULOSE (5000 MPA.S AT 1%); .ALPHA.-TOCOPHEROL ACETATE, DL-; GLYCERIN; ALMOND OIL; STEARIC ACID; DIISOSTEARYL MALATE; NEOPENTYL GLYCOL DIHEPTANOATE; ISODODECANE; WATER; WATERMELON; APPLE; LENS CULINARIS FRUIT; SODIUM LACTATE; SODIUM PYRROLIDONE CARBOXYLATE; EUCALYPTUS OIL; GLYCOL DISTEARATE; ETHYLHEXYLGLYCERIN; MALTODEXTRIN; PHENOXYETHANOL; GLYCERYL STEARATE CITRATE; HEXYLENE GLYCOL; VITIS VINIFERA SEED; ISOMALT; SAPONARIA OFFICINALIS LEAF; KIWI FRUIT; SWERTIA CHIRAYITA WHOLE; LECITHIN, SOYBEAN

ASYSTEM Daily Defense Moisturizer + SPF 30

Drug Facts

Active Ingredient....................Purpose

Homosalate 8.00%..................Sunscreen

Octilsalate 5.00%..................Sunscreen

Octocrylene 5.50%..................Sunscreen

Avobenxone 3.00%..................Sunscreen

Uses

Helps prevent sunburn. If used as directed with other sun protection measures, (see Directions), decreases the risk of skin cancer and early skin aging caused by the sun.

Warnings

For external use only.

Do not use on broken or damaged skin.

When using the product keep out of eyes.

Rinse with water to remove.

Seek out a doctor if rash occurs.

Keep out of reach of children. If product is swallowed, call a doctor or poison control center immediately.

Directions

Apply liberally 15 minutes before sun exposure.

Reapply at least every 2 hours, as well as after 40 minutes of sweating, immediately after towel drying.

Sun Protection Measures:

Spending time in the sun increases your risk of skin cancer and early skin aging. To decrease this risk, regularly use a sunscreen with a least a broad spectrum SPF of 15 or higher and other sun protecting measures including: limiting time in the sun, especially from 10am-2pm, and wearing long-sleeved shirts, pants, hats and sunglasses.

For children under 8 months, ask a doctor.

Inactive Ingredients

Aqua (Water), C12-15 Alkyl Benzoate, Glycerin, Diisostearyl Malate, Glyceryl Stearate Citrate, Stearic Acid, Glycol Distearate, Ethylhexylglycerin, Hexylene Glycol, Xanthan Gum, Prunus Amygdalus Dulcia (Sweet Almond) Oil, Actinidia Chinensis (Kiwi) Fruit Extract, Cyanidium Caldarium Extract, Saponaria Pumila Callus Culture Extract, Isomalt, Lecithin, Maltodextrin, Swertia Chirata Leaf Extract, Vitis Vinifera (Grape) Juice Extract, Glycerin, Citrus Vulgaris (Watermelon) Fruit Extract, Pyrus Malus (Apple) Fruit Extract, Lens Esculenta (Lentil) Fruit Extract, Sodium PCA, Sodium Lactate, Tocopheryl Acetate, Hydoxyethylcellulose, Eucalyptus Globulus Leaf Oil, Citrus Aurantium Bergamia (Bergamot) Fruit Oil

Other Information

Protect this product from excessive heat and direct sun.

Questions?

info@asystem.com